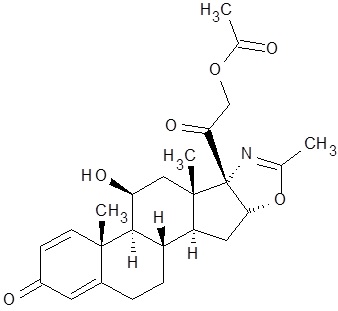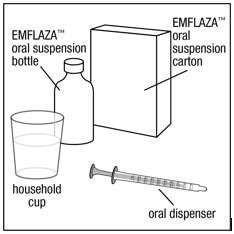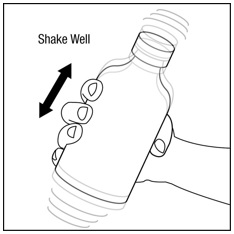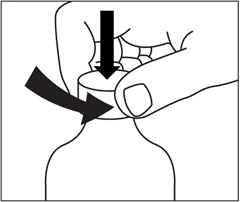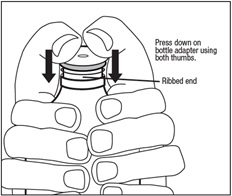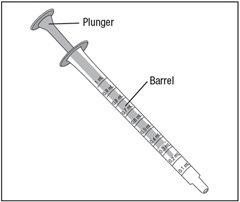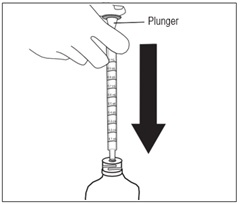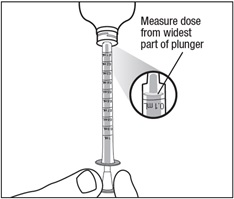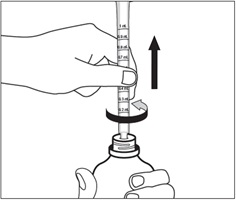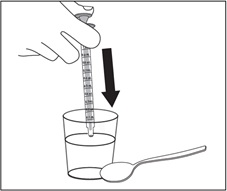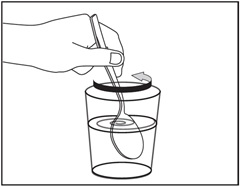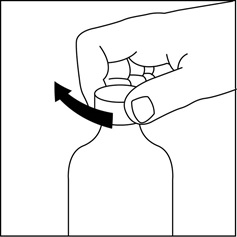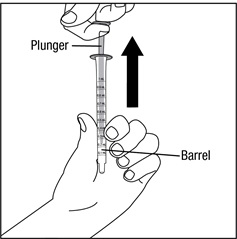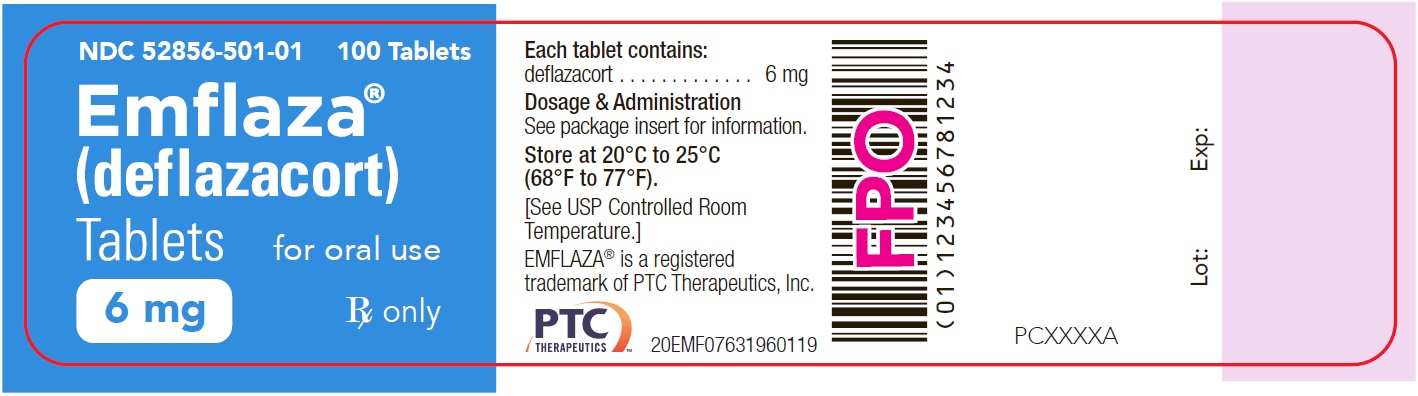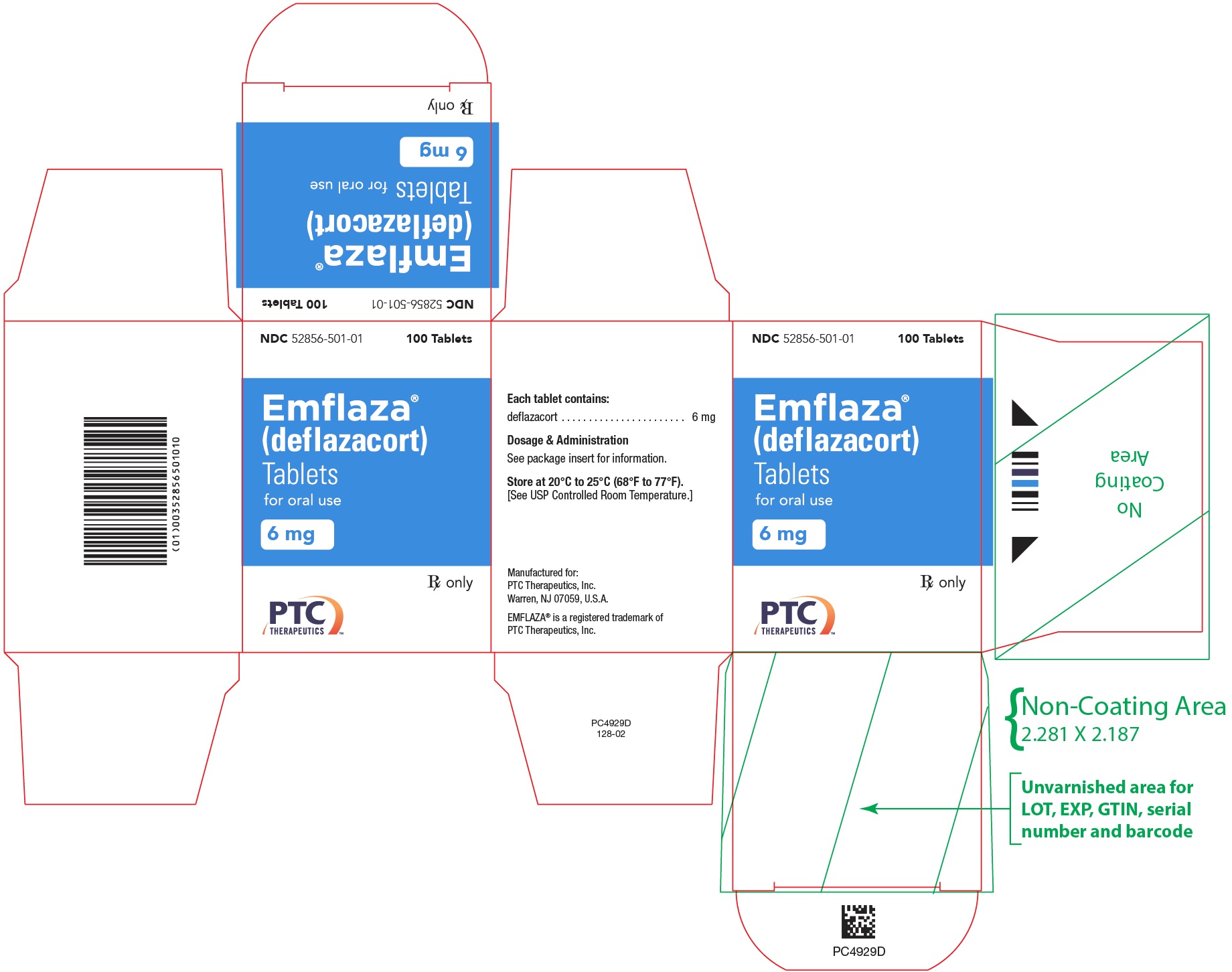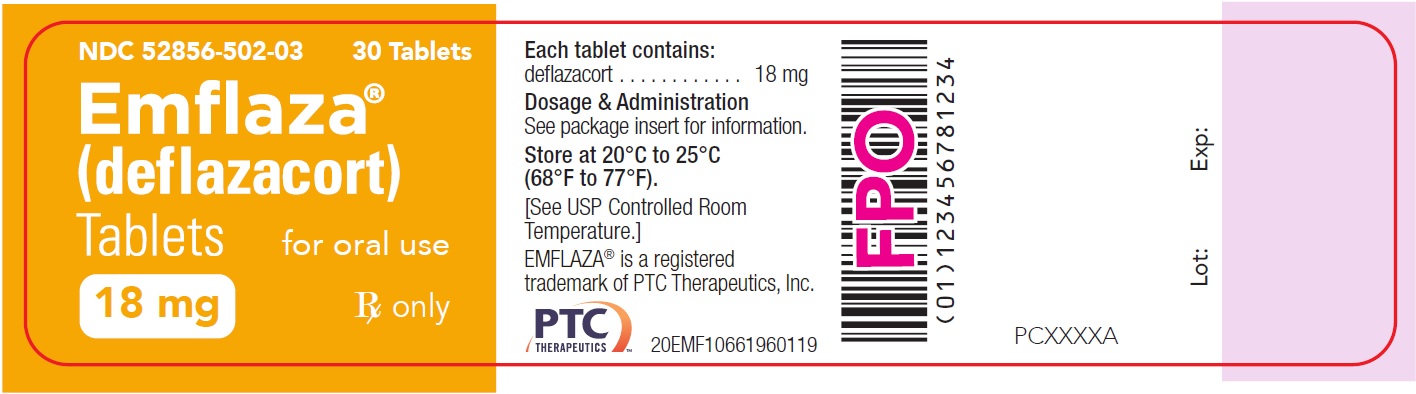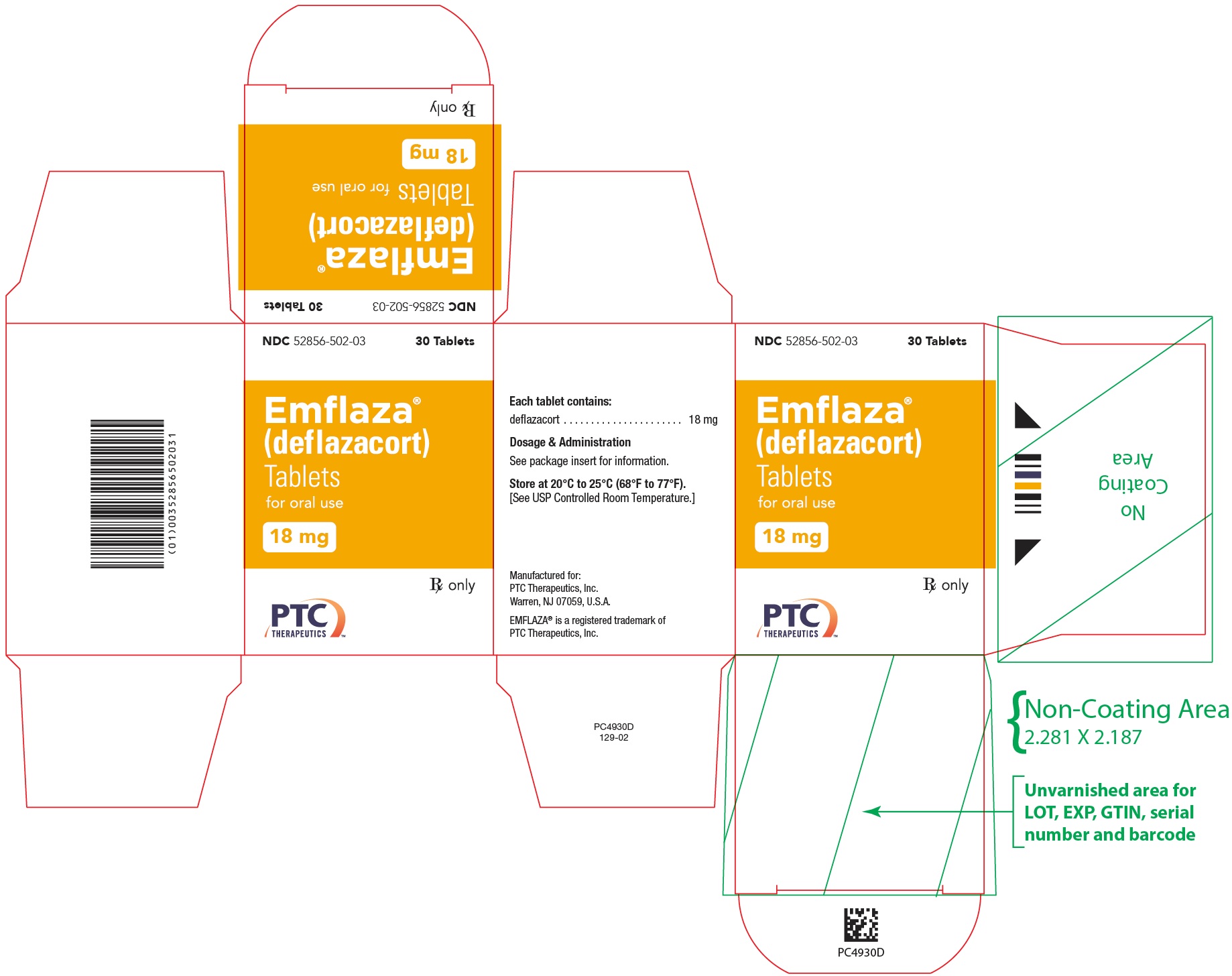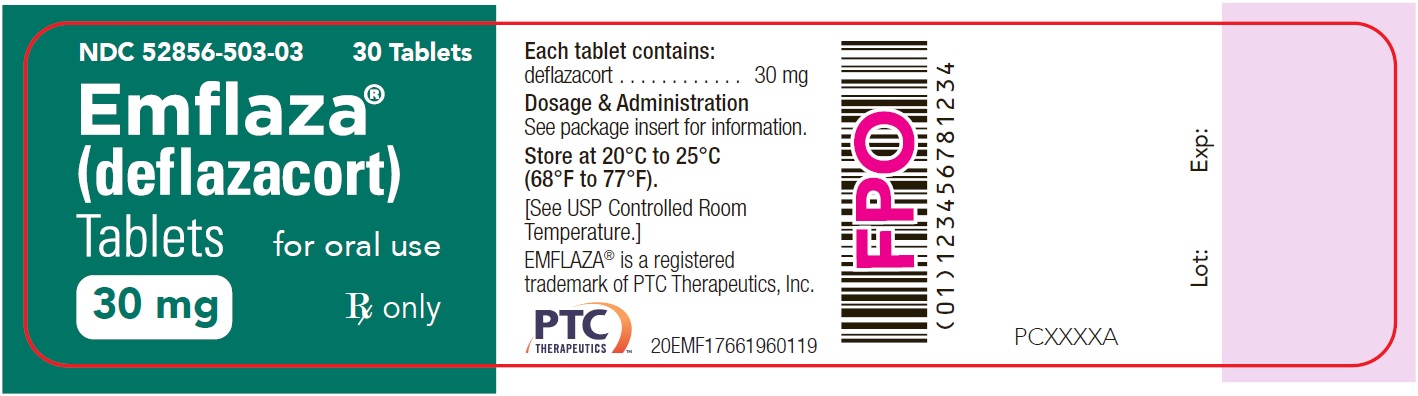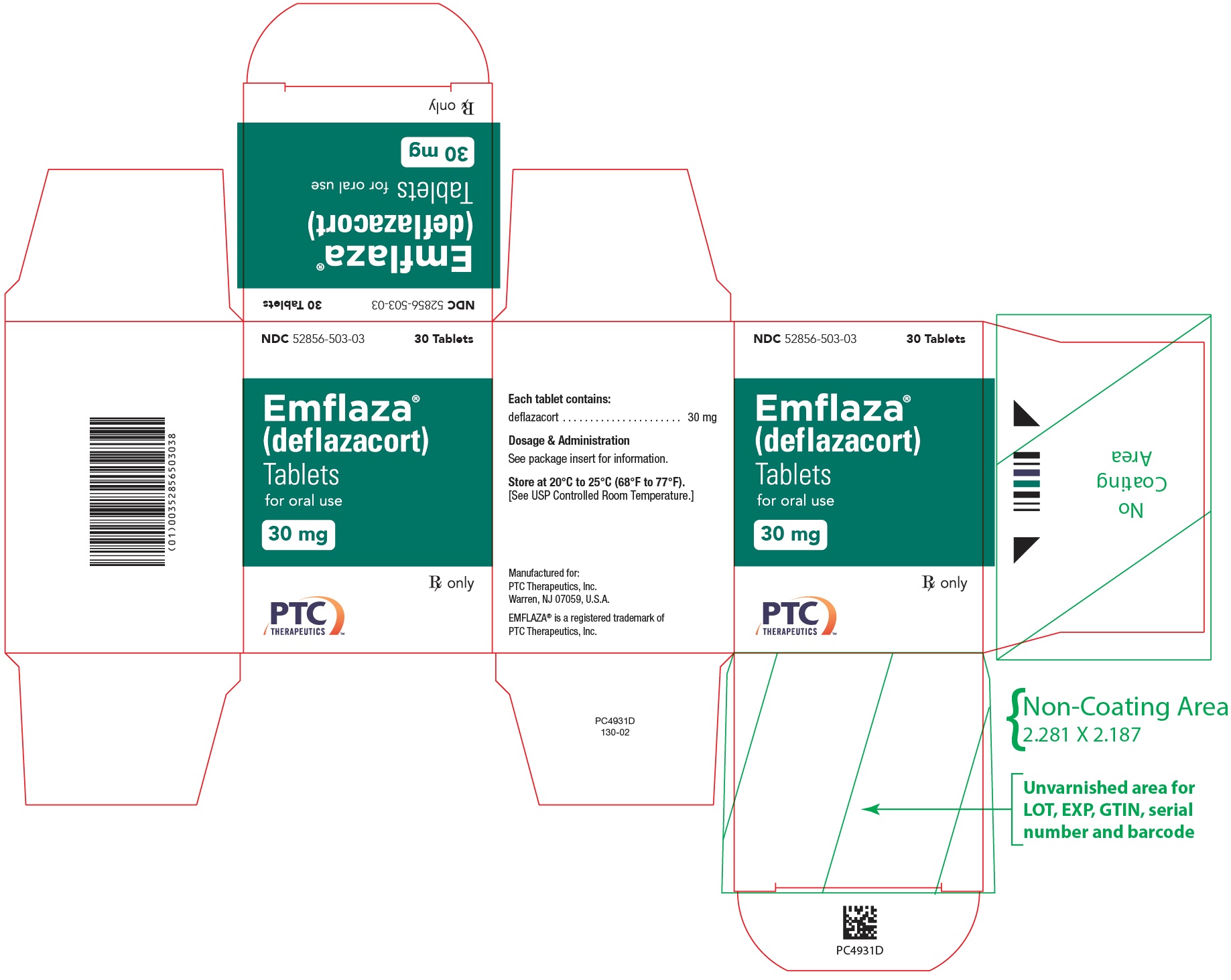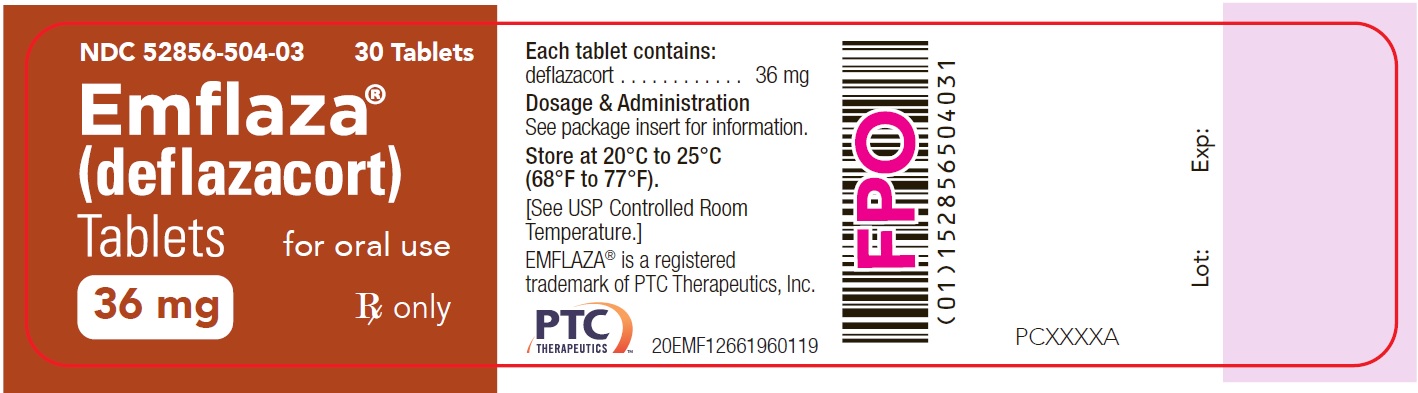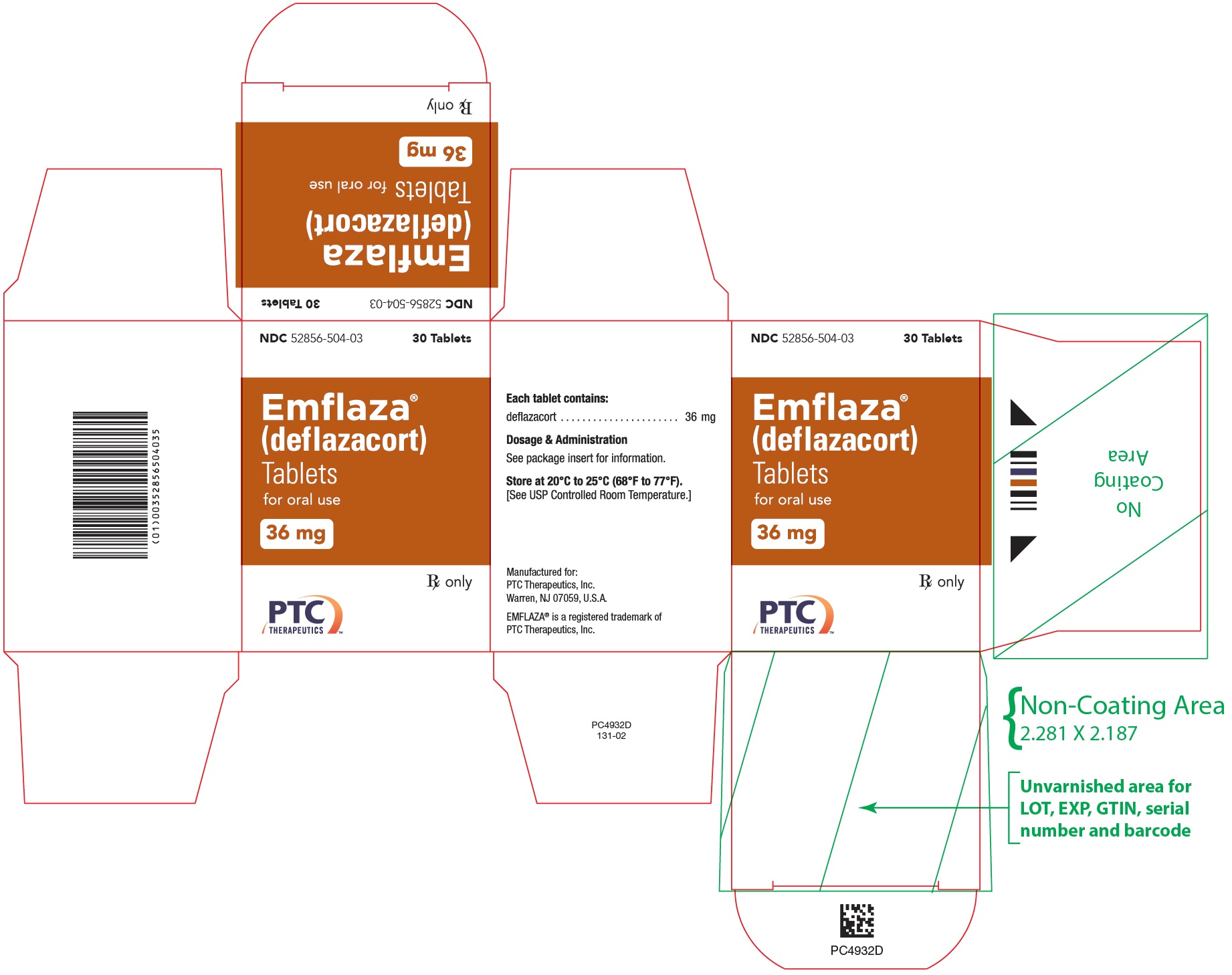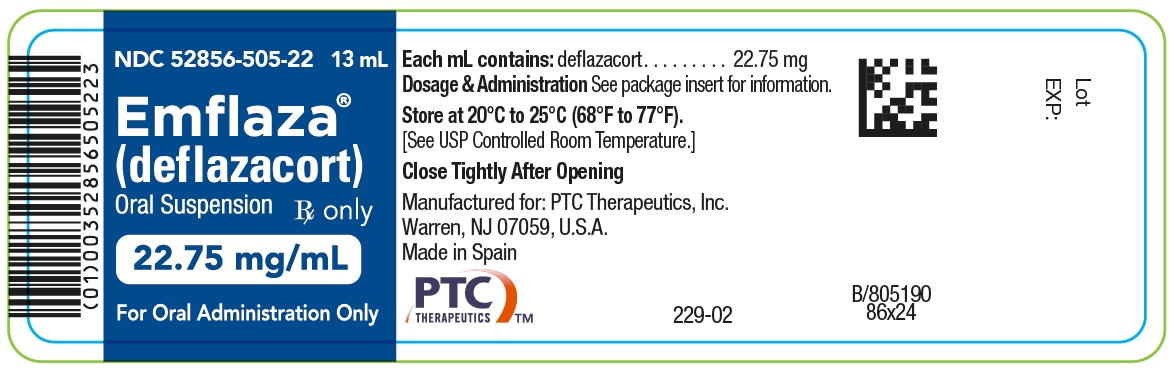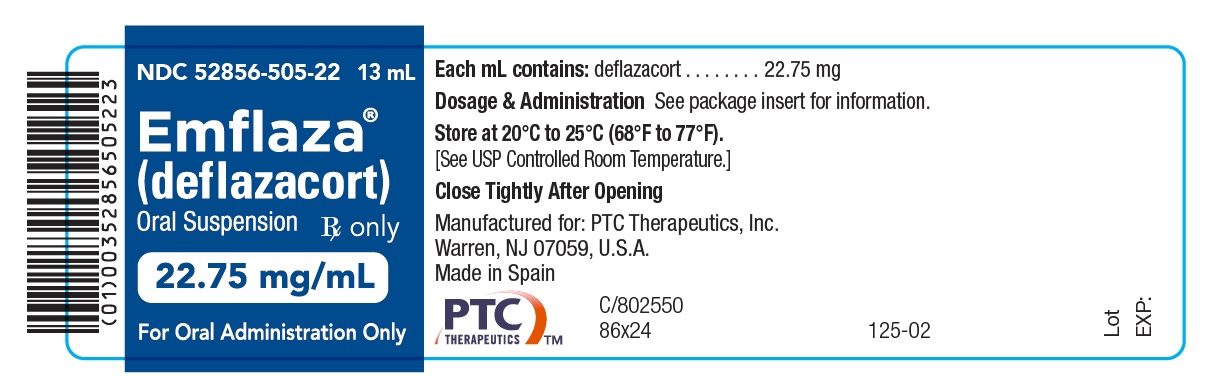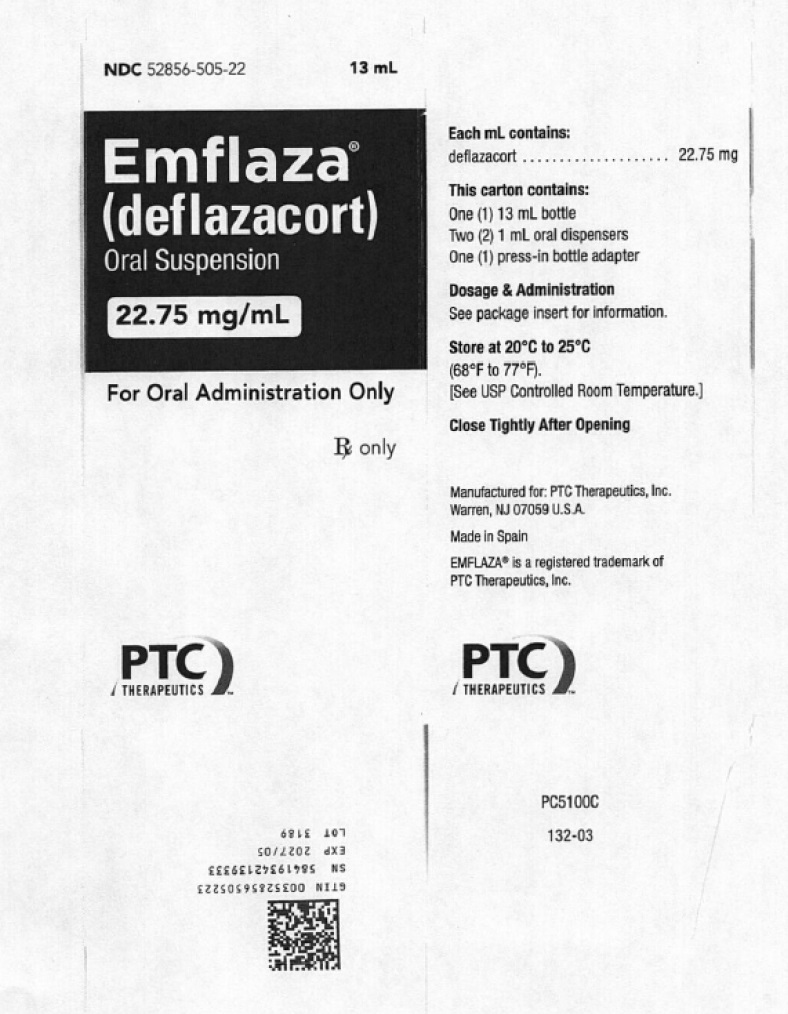 DRUG LABEL: EMFLAZA
NDC: 52856-501 | Form: TABLET
Manufacturer: PTC Therapeutics, Inc.
Category: prescription | Type: HUMAN PRESCRIPTION DRUG LABEL
Date: 20251113

ACTIVE INGREDIENTS: DEFLAZACORT 6 mg/1 1
INACTIVE INGREDIENTS: SILICON DIOXIDE; LACTOSE MONOHYDRATE; MAGNESIUM STEARATE; STARCH, PREGELATINIZED CORN

HIGHLIGHTS OF PRESCRIBING INFORMATION

These highlights do not include all the information needed to use EMFLAZA® safely and effectively. See full prescribing information for EMFLAZA.
EMFLAZA® (deflazacort) tablets, for oral use
EMFLAZA® (deflazacort) oral suspension
Initial U.S. Approval: 2017

RECENT MAJOR CHANGES

Warnings and Precautions

Immunosuppression and Increased Risk of Infection (5.2) 06/2024

1 INDICATIONS AND USAGE

EMFLAZA is a corticosteroid indicated for the treatment of Duchenne muscular dystrophy (DMD) in patients 2 years of age and older (1)

2 DOSAGE AND ADMINISTRATION

- The recommended once-daily dosage is approximately 0.9 mg/kg/day administered orally (2.2)
- Discontinue gradually when administered for more than a few days (2.3)

3 DOSAGE FORMS AND STRENGTHS

- Tablets: 6 mg, 18 mg, 30 mg, and 36 mg (3)
- Oral Suspension: 22.75 mg/mL (3)

4 CONTRAINDICATIONS

Hypersensitivity to deflazacort or any of the inactive ingredients in EMFLAZA (4)

5 WARNINGS AND PRECAUTIONS

- Alterations in Endocrine Function: Hypothalamic-pituitary-adrenal axis suppression, Cushing’s syndrome, and hyperglycemia can occur; Monitor patients for these conditions with chronic use of EMFLAZA (2.3, 5.1)
- Immunosuppression and Increased Risk of Infection: Increased risk of new, exacerbation, dissemination, or reactivation of latent infections, which can be severe and at times fatal; Signs and symptoms of infection may be masked (5.2)
- Alterations in Cardiovascular/Renal Function: Monitor for elevated blood pressure and sodium, and for decreased potassium levels (5.3)
- Gastrointestinal Perforation: Increased risk in patients with certain GI disorders; Signs and symptoms may be masked (5.4)
- Behavioral and Mood Disturbances: May include euphoria, insomnia, mood swings, personality changes, severe depression, and psychosis (5.5)
- Effects on Bones: Monitor for decreases in bone mineral density with chronic use of EMFLAZA (5.6)
- Ophthalmic Effects: May include cataracts, infections, and glaucoma; Monitor intraocular pressure if EMFLAZA is continued for more than 6 weeks (5.7)
- Vaccination: Do not administer live or live attenuated vaccines to patients receiving immunosuppressive doses of corticosteroids. Administer live-attenuated or live vaccines at least 4 to 6 weeks prior to starting EMFLAZA (5.8)
- Serious Skin Rashes: Discontinue at the first sign of rash, unless the rash is clearly not drug related (5.9)

6 ADVERSE REACTIONS

The most common adverse reactions (≥ 10% for EMFLAZA and greater than placebo) are Cushingoid appearance, weight increased, increased appetite, upper respiratory tract infection, cough, pollakiuria, hirsutism, central obesity, and nasopharyngitis (6.1)

To report SUSPECTED ADVERSE REACTIONS, contact PTC Therapeutics, Inc. at 1-866-562-4620 or Pharmacovigilance@PTCBio.com or FDA at 1-800-FDA-1088 or www.fda.gov/medwatch.

7 DRUG INTERACTIONS

- Moderate or strong CYP3A4 inhibitors: Give one third of the recommended dosage of EMFLAZA (7.1)
- Avoid use of moderate or strong CYP3A4 inducers with EMFLAZA, as they may reduce efficacy (7.1)

FULL PRESCRIBING INFORMATION

1 INDICATIONS AND USAGE

EMFLAZA is indicated for the treatment of Duchenne muscular dystrophy (DMD) in patients 2 years of age and older.

2 DOSAGE AND ADMINISTRATION

2.1 Assessments Prior to First Dose of EMFLAZA

Administer all immunizations according to immunization guidelines prior to starting EMFLAZA. Administer live-attenuated or live vaccines at least 4 to 6 weeks prior to starting EMFLAZA [see Warnings and Precautions (5.8)].

2.2 Dosing Information

The recommended oral dosage of EMFLAZA is approximately 0.9 mg/kg/day once daily. If tablets are used, round up to the nearest possible dose. Any combination of the four EMFLAZA tablet strengths can be used to achieve this dose. If the oral suspension is used, round up to the nearest tenth of a milliliter (mL).

2.3 Discontinuation

Dosage of EMFLAZA must be decreased gradually if the drug has been administered for more than a few days [see Warnings and Precautions (5.1)].

2.4 Important Preparation and Administration Instructions

EMFLAZA Tablets and Oral Suspension can be taken with or without food. Do not administer EMFLAZA with grapefruit juice [see Drug Interactions (7.1)]

EMFLAZA Tablets
EMFLAZA Tablets can be administered whole or crushed and taken immediately after mixing with applesauce.

EMFLAZA Oral Suspension
Shake EMFLAZA Oral Suspension well before administration.

Use only the oral dispenser provided with the product. After withdrawing the appropriate dose into the oral dispenser, slowly add the EMFLAZA Oral Suspension into 3 to 4 ounces of juice (except grapefruit juice) or milk and mix well. The dose should then be administered immediately.

Discard any unused EMFLAZA Oral Suspension remaining after 1 month of first opening the bottle.

2.5 Dosage Modification for Use with CYP3A4 Inhibitors and Inducers

CYP3A4 Inhibitors
Give one third of the recommended dosage when EMFLAZA is administered with moderate or strong CYP3A4 inhibitors. For example, a 36 mg per day dose would be reduced to a 12 mg per day dose when used with moderate or strong CYP3A4 inhibitors [see Drug Interactions (7.1) and Clinical Pharmacology (12.3)].

CYP3A4 Inducers
Avoid use with moderate or strong CYP3A4 inducers with EMFLAZA [see Drug Interactions (7.1) and Clinical Pharmacology (12.3)].

3 DOSAGE FORMS AND STRENGTHS

Tablets

- 6 mg: White and round with “6” debossed on one side
- 18 mg: White and round with “18” debossed on one side
- 30 mg: White and oval with “30” debossed on one side
- 36 mg: White and oval with “36” debossed on one side

Oral Suspension

- 22.75 mg/mL: Whitish suspension

4 CONTRAINDICATIONS

EMFLAZA is contraindicated in patients with known hypersensitivity to deflazacort or to any of the inactive ingredients. Instances of hypersensitivity, including anaphylaxis, have occurred in patients receiving corticosteroid therapy [see Warnings and Precautions (5.15) and Adverse Reactions (6.2)].

5 WARNINGS AND PRECAUTIONS

5.1 Alterations in Endocrine Function

Corticosteroids, such as EMFLAZA, can cause serious and life-threatening alterations in endocrine function, especially with chronic use. Monitor patients receiving EMFLAZA for Cushing’s syndrome, hyperglycemia, and adrenal insufficiency after EMFLAZA withdrawal. In addition, patients with hypopituitarism, primary adrenal insufficiency or congenital adrenal hyperplasia, altered thyroid function, or pheochromocytoma may be at increased risk for adverse endocrine events.

Risk of Adrenal Insufficiency Following Corticosteroid Withdrawal
Corticosteroids produce reversible hypothalamic-pituitary-adrenal (HPA) axis suppression, with the potential for the development of secondary adrenal insufficiency after withdrawal of corticosteroid treatment. Acute adrenal insufficiency can occur if corticosteroids are withdrawn abruptly, and can be fatal. The degree and duration of adrenocortical insufficiency produced is variable among patients and depends on the dose, frequency, and duration of corticosteroid therapy. The risk is reduced by gradually tapering the corticosteroid dose when withdrawing treatment. This insufficiency may persist, however, for months after discontinuation of prolonged therapy; therefore, in any situation of stress occurring during that period of discontinuation, corticosteroid therapy should be reinstituted. For patients already taking corticosteroids during times of stress, the dosage may need to be increased.

A steroid “withdrawal syndrome”, seemingly unrelated to adrenocortical insufficiency, may also occur following abrupt discontinuance of corticosteroids. This syndrome includes symptoms such as anorexia, nausea, vomiting, lethargy, headache, fever, joint pain, desquamation, myalgia, and/or weight loss. These effects are thought to be due to the sudden change in corticosteroid concentration rather than to low corticosteroid levels.

Cushing’s Syndrome
Cushing’s syndrome (hypercortisolism) occurs with prolonged exposure to exogenous corticosteroids, including EMFLAZA. Symptoms include hypertension, truncal obesity and thinning of the limbs, purple striae, facial rounding, facial plethora, muscle weakness, easy and frequent bruising with thin fragile skin, posterior neck fat deposition, osteopenia, acne, amenorrhea, hirsutism and psychiatric abnormalities.

Hyperglycemia
Corticosteroids can increase blood glucose, worsen pre-existing diabetes, predispose those on long-term therapy to diabetes mellitus, and may reduce the effect of anti-diabetic drugs. Monitor blood glucose at regular intervals. For patients with hyperglycemia, anti-diabetic treatment should be initiated or adjusted accordingly.

Considerations for Use in Patients with Altered Thyroid Function
Metabolic clearance of corticosteroids is decreased in hypothyroid patients and increased in hyperthyroid patients. Changes in thyroid status of the patient may necessitate a dose adjustment of the corticosteroid. When concomitant administration of corticosteroids and levothyroxine is required, administration of corticosteroid should precede the initiation of levothyroxine therapy to reduce the risk of adrenal crisis.

Pheochromocytoma Crisis
There have been reports of pheochromocytoma crisis, which can be fatal, after administration of systemic corticosteroids. In patients with suspected or identified pheochromocytoma, consider the risk of pheochromocytoma crisis prior to administering corticosteroids.

5.2 Immunosuppression and Increased Risk of Infection

Corticosteroids, including EMFLAZA, suppress the immune system and increase the risk of infection with any pathogen, including viral, bacterial, fungal, protozoan, or helminthic pathogens. Corticosteroids can:

- Reduce resistance to new infections
- Exacerbate existing infections
- Increase the risk of disseminated infections
- Increase the risk of reactivation or exacerbation of latent infections
- Mask some signs of infections

Corticosteroid-associated infections can be mild but can be severe, and at times fatal. The rate of infectious complications increases with increasing corticosteroid dosages.

Monitor for the development of infection and consider EMFLAZA withdrawal or dosage reduction as needed.

Tuberculosis

If EMFLAZA is used to treat a condition in patients with latent tuberculosis or tuberculin reactivity, reactivation of tuberculosis may occur. Closely monitor such patients for reactivation. During prolonged EMFLAZA therapy, patients with latent tuberculosis or tuberculin reactivity should receive chemoprophylaxis.

Varicella Zoster and Measles Viral Infections

Varicella and measles can have a serious or even fatal course in non-immune patients taking corticosteroids, including EMFLAZA. In corticosteroid-treated patients who have not had these diseases or are non-immune, particular care should be taken to avoid exposure to varicella and measles.

- If an EMFLAZA-treated patient is exposed to varicella, prophylaxis with varicella zoster immunoglobulin may be indicated. If varicella develops, treatment with antiviral agents may be considered.
- If an EMFLAZA-treated patient is exposed to measles, prophylaxis with immunoglobulin may be indicated.

Hepatitis B Virus Reactivation

Hepatitis B virus reactivation can occur in patients who are hepatitis B carriers treated with immunosuppressive dosages of corticosteroids, including EMFLAZA. Reactivation can also occur infrequently in corticosteroid-treated patients who appear to have resolved hepatitis B infection.

Screen patients for hepatitis B infection before initiating immunosuppressive (e.g., prolonged) treatment with EMFLAZA. For patients who show evidence of hepatitis B infection, recommend consultation with physicians with expertise in managing hepatitis B regarding monitoring and consideration for hepatitis B antiviral therapy.

Fungal Infections

Corticosteroids, including EMFLAZA, may exacerbate systemic fungal infections; therefore, avoid EMFLAZA use in the presence of such infections unless EMFLAZA is needed to control drug reactions. For patients on chronic EMFLAZA therapy who develop systemic fungal infections, EMFLAZA withdrawal or dose reduction is recommended.

Amebiasis

Corticosteroids, including EMFLAZA, may activate latent amebiasis. Therefore, it is recommended that latent amebiasis or active amebiasis be ruled out before initiating EMFLAZA in patients who have spent time in the tropics or patients with unexplained diarrhea.

Strongyloides Infestation

Corticosteroids, including EMFLAZA, should be used with great care in patients with known or suspected Strongyloides (threadworm) infestation. In such patients, corticosteroid-induced immunosuppression may lead to Strongyloides hyperinfection and dissemination with widespread larval migration, often accompanied by severe enterocolitis and potentially fatal gram-negative septicemia.

Cerebral Malaria

Avoid corticosteroids, including EMFLAZA, in patients with cerebral malaria.

5.3 Alterations in Cardiovascular/Renal Function

Corticosteroids, including EMFLAZA, can cause elevation of blood pressure, salt, and water retention, and increased excretion of potassium and calcium. Monitor blood pressure and assess for signs and symptoms of volume overload. Monitor serum potassium levels. Dietary salt restriction and potassium supplementation may be necessary. EMFLAZA should be used with caution in patients with congestive heart failure, hypertension, or renal insufficiency.

Literature reports suggest an association between use of corticosteroids and left ventricular free wall rupture after a recent myocardial infarction; therefore, therapy with EMFLAZA should be used with great caution in these patients.

5.4 Gastrointestinal Perforation

There is an increased risk of gastrointestinal perforation during corticosteroid use in patients with certain gastrointestinal disorders such as active or latent peptic ulcers, diverticulitis, fresh intestinal anastomoses, and non-specific ulcerative colitis. Signs of gastrointestinal perforation, such as peritoneal irritation, may be masked in patients receiving corticosteroids.

Avoid corticosteroids if there is a probability of impending perforation, abscess, or other pyogenic infections; diverticulitis; fresh intestinal anastomoses; or active or latent peptic ulcer.

5.5 Behavioral and Mood Disturbances

Potentially severe psychiatric adverse reactions may occur with systemic corticosteroids, including EMFLAZA. Symptoms typically emerge within a few days or weeks of starting treatment and may be dose-related. These reactions may improve after either dose reduction or withdrawal, although pharmacologic treatment may be necessary. Psychiatric adverse reactions usually involve hypomanic or manic symptoms (e.g., euphoria, insomnia, mood swings) during treatment and depressive episodes after discontinuation of treatment. Inform patients or caregivers of the potential for behavioral and mood changes and encourage them to seek medical attention if psychiatric symptoms develop, especially if depressed mood or suicidal ideation is suspected.

5.6 Effects on Bones

Decreased Bone Mineral Density
Corticosteroids, including EMFLAZA, decrease bone formation and increase bone resorption both through their effect on calcium regulation (i.e., decreasing absorption and increasing excretion) and inhibition of osteoblast function. This, together with a decrease in the protein matrix of the bone secondary to an increase in protein catabolism and reduced sex hormone production, may lead to inhibition of bone growth in pediatric patients and the development of bone loss at any age. Bone loss can predispose patients to vertebral and long bone fractures. Consider a patient’s risk of osteoporosis before initiating corticosteroid therapy. Monitor bone mineral density in patients on long-term treatment with EMFLAZA.

Avascular Necrosis
Corticosteroids, including EMFLAZA, may cause avascular necrosis.

5.7 Ophthalmic Effects

Use of corticosteroids, including EMFLAZA, may produce posterior subcapsular cataracts. Corticosteroids may also cause glaucoma with possible damage to the optic nerves, and may increase the risk of secondary ocular infections caused by bacteria, fungi, or viruses. Corticosteroids are not recommended for patients with active ocular herpes simplex.

Intraocular pressure may become elevated in some patients taking corticosteroids. If treatment with EMFLAZA is continued for more than 6 weeks, monitor intraocular pressure.

5.8 Immunizations

Administer all immunizations according to immunization guidelines prior to starting EMFLAZA. Administer live-attenuated or live vaccines at least 4 to 6 weeks prior to starting EMFLAZA. Patients on EMFLAZA may receive concurrent vaccinations, except for live-attenuated or live vaccines.

5.9 Serious Skin Rashes

Toxic epidermal necrolysis has been reported with the use of deflazacort with symptoms beginning within 8 weeks of starting treatment. Discontinue at the first sign of rash, unless the rash is clearly not drug related.

5.10 Effects on Growth and Development

Long-term use of corticosteroids, including EMFLAZA, can have negative effects on growth and development in children.

5.11 Myopathy

Patients receiving corticosteroids, including EMFLAZA, and concomitant therapy with neuromuscular blocking agents (e.g., pancuronium) or patients with disorders of neuromuscular transmission (e.g., myasthenia gravis) may be at increased risk of developing acute myopathy. This acute myopathy is generalized, may involve ocular and respiratory muscles, and may result in quadriparesis. Elevation of creatine kinase may occur. Clinical improvement or recovery after stopping corticosteroids may require weeks to years.

5.12 Kaposi’s Sarcoma

Kaposi’s sarcoma has been reported to occur in patients receiving corticosteroid therapy, most often for chronic conditions. Discontinuation of corticosteroids may result in clinical improvement of Kaposi’s sarcoma.

5.13 Risk of Serious Adverse Reactions in Infants because of Benzyl Alcohol Preservative

EMFLAZA Oral Suspension contains benzyl alcohol and is not approved for use in pediatric patients less than 2 years of age. Serious and fatal adverse reactions including “gasping syndrome” can occur in neonates and low birth weight infants treated with benzyl alcohol-preserved drugs, including EMFLAZA. The “gasping syndrome” is characterized by central nervous system depression, metabolic acidosis, and gasping respirations.
When prescribing EMFLAZA Oral Suspension, consider the combined daily metabolic load of benzyl alcohol from all sources, including EMFLAZA Oral Suspension (EMFLAZA Oral Suspension contains 10.45 mg of benzyl alcohol per mL; EMFLAZA Tablets do not contain benzyl alcohol) and other drugs containing benzyl alcohol. The minimum amount of benzyl alcohol at which serious adverse reactions may occur is not known. At the recommended dose of 0.9 mg/kg/day of EMFLAZA Oral Suspension, patients would receive approximately 0.4 mg/kg/day of benzyl alcohol [see Use in Specific Populations (8.4)].

5.14 Thromboembolic Events

Observational studies have shown an increased risk of thromboembolism (including venous thromboembolism) particularly with higher cumulative doses of corticosteroids. It is unclear if risk differs by daily dose or duration of use. Use EMFLAZA with caution in patients who have or may be predisposed to thromboembolic disorders.

5.15 Anaphylaxis

Rare instances of anaphylaxis have occurred in patients receiving corticosteroid therapy, including EMFLAZA.

6 ADVERSE REACTIONS

The following serious adverse reactions are discussed in more detail in other sections:

- Alterations in Endocrine Function [see Warnings and Precautions (5.1)]
- Immunosuppression and Increased Risk of Infection [see Warnings and Precautions (5.2)]
- Alterations in Cardiovascular/Renal Function [see Warnings and Precautions (5.3)]
- Gastrointestinal Perforation [see Warnings and Precautions (5.4)]
- Behavioral and Mood Disturbances [see Warnings and Precautions (5.5)]
- Effects on Bones [see Warnings and Precautions (5.6)]
- Ophthalmic Effects [see Warnings and Precautions (5.7)]
- Immunizations [see Warnings and Precautions (5.8)]
- Serious Skin Rashes [see Warnings and Precautions (5.9)]
- Effects on Growth and Development [see Warnings and Precautions (5.10)]
- Myopathy [see Warnings and Precautions (5.11)]
- Kaposi’s Sarcoma [see Warnings and Precautions (5.12)]
- Risk of Serious Adverse Reactions in Infants because of Benzyl Alcohol Preservative [see Warnings and Precautions (5.13)]
- Thromboembolic Events [see Warnings and Precautions (5.14)]
- Anaphylaxis [see Warnings and Precautions (5.15)]

6.1 Clinical Trials Experience

Because clinical trials are conducted under widely varying conditions, adverse reaction rates observed in the clinical trials of a drug cannot be directly compared to rates in the clinical trials of another drug and may not reflect the rates observed in practice.

In Study 1 [see Clinical Studies (14)], the adverse reactions that were associated with deflazacort treatment discontinuation, in decreasing order of frequency, were weight increased, obesity, cataract, and sleep disorder.

Most Common Adverse Reactions in Clinical Studies
Table 1 lists the adverse reactions that occurred in ≥ 5% of patients in the 0.9 mg/kg/day deflazacort-treated group and that occurred more frequently than in placebo patients in Study 1, which included patients with DMD between the ages of 5 and 15 years.

Table 1: Adverse Reactions that Occurred in ≥ 5% of Deflazacort-Treated Patients and Occurred More Frequently than in Placebo Patients with DMD (Study 1)
Adverse Reaction | Deflazacort 0.9 mg/kg/d (N=51) % at 12 weeks | Placebo (N=50) % at 12 weeks^1
Cushingoid appearance | 33 | 12
Weight increased | 20 | 6
Increased appetite | 14 | 2
Upper respiratory tract infection | 12 | 10
Cough | 12 | 6
Pollakiuria | 12 | 2
Nasopharyngitis | 10 | 6
Hirsutism | 10 | 2
Central obesity | 10 | 4
Erythema | 8 | 6
Irritability | 8 | 4
Rhinorrhea | 8 | 0
Abdominal discomfort | 6 | 2
^1 At 12 weeks placebo patients were re-randomized to receive either deflazacort or an active comparator.

Common adverse reactions (≥ 5% of deflazacort-treated patients) that occurred over 52 weeks of exposure to deflazacort 0.9 mg/kg/day in Study 1 and at a higher rate than deflazacort 0.9 mg/kg/day in the 12-week placebo-controlled phase of the trial include Cushingoid appearance (60%), hirsutism (35%), weight increased (28%), erythema (28%), central obesity (25%), abdominal pain/abdominal pain upper (18% combined), pollakiuria (15%), constipation (10%), irritability (10%), abnormal behavior (9%), pyrexia (9%), back pain (7%), rash (7%), contusion (6%), nausea (6%), psychomotor hyperactivity (6%), epistaxis (6%), and skin striae (6%).

Study 1 also evaluated a higher dosage of deflazacort (1.2 mg/kg/day). Compared with the 0.9 mg/kg/day dosage, deflazacort 1.2 mg/kg/day over 52 weeks was associated with a higher incidence of certain adverse reactions, including Cushingoid appearance (69%), erythema (49%), hirsutism (37%), headache (34%), weight increased (32%), constipation (15%), abdominal pain upper (14%), skin striae (11%), acne (11%), and abdominal discomfort (8%). As there was no additional benefit with the 1.2 mg/kg/day dose of deflazacort, use of EMFLAZA 1.2 mg/kg/day is not recommended for the treatment of DMD [see Dosage and Administration (2.2)].

In an additional clinical study of two years duration with extended follow-up (Study 2), many of the same adverse reactions were observed. In addition, musculoskeletal events associated with long-term steroid use were also observed, including muscle weakness, tendon disorder, and osteopenia.

Less Common Adverse Reactions Observed in Clinical Studies
Other adverse reactions (≥ 1% frequency in any deflazacort treatment group and greater than placebo) that were observed during the 12-week placebo-controlled phase of Study 1 are shown below.

Eye Disorders: Lacrimation increased

Gastrointestinal Disorders: Dyspepsia, nausea, gastrointestinal disorder

General Disorders and Administration Site Conditions: Thirst

Infections: Hordeolum, impetigo, influenza, otitis externa, pharyngitis, tooth abscess, urinary tract infection, viral infection

Injury, Poisoning and Procedural Complications: Back injury, contusion, face injury, fibula fracture, greenstick fracture, heat exhaustion

Investigations: Glucose urine present, heart rate irregular

Musculoskeletal and Connective Tissue Disorders: Back pain, muscle spasms, myalgia, neck mass, neck pain, pain in extremity

Nervous System Disorders: Dizziness, psychomotor hyperactivity

Psychiatric Disorders: Affect lability, aggression, depression, emotional disorder, middle insomnia, mood altered, mood swings, sleep disorder

Renal and Urinary Disorders: Chromaturia, dysuria, hypertonic bladder

Reproductive System and Breast Disorders: Testicular pain

Respiratory, Thoracic, and Mediastinal Disorders: Hypoventilation, rhinorrhea

Skin and Subcutaneous Tissue Disorders: Acne, alopecia, dermatitis acneiform

Vascular Disorders: Hot flush

6.2 Postmarketing Experience

The following adverse reactions have been reported during post-approval use of deflazacort worldwide or during post-approval use of other corticosteroids. These reactions are reported voluntarily from a population of uncertain size; therefore, it is not always possible to estimate their frequency or establish a causal relationship to drug exposure.

Blood and Lymphatic System Disorders: Leukocytosis

Cardiac Disorder: Heart failure

Eye Disorders: Chorioretinopathy, corneal or scleral thinning

Gastrointestinal Disorders: Acute pancreatitis (especially in children), hemorrhage, peptic ulceration, perforation of peptic ulcer

General Disorders and Administration Site Conditions: Edema, impaired healing

Immune System Disorders: Hypersensitivity including anaphylaxis

Metabolism and Nutrition Disorders: Impaired carbohydrate tolerance with increased requirement for anti-diabetic therapy, negative protein and calcium balance, potassium loss and hypokalemic alkalosis when co-administered with beta 2-agonist and xanthines

Musculoskeletal and Connective Tissue Disorders: Avascular necrosis, muscle wasting, negative nitrogen balance, tendonitis and tendon rupture when co-administered with quinolones, vertebral and long bone fractures

Nervous System Disorders: Aggravation of epilepsy, increased intra-cranial pressure with papilledema in children (pseudotumor cerebri) usually after treatment withdrawal, vertigo

Psychiatric Disorders: Anxiety, cognitive dysfunction including confusion and amnesia, delusions, hallucinations, mania, suicidal thoughts

Skin and Subcutaneous Tissue Disorders: Toxic epidermal necrolysis

Vascular Disorders: Thromboembolism, in particular in patients with underlying conditions associated with increased thrombotic tendency, benign intracranial hypertension

7 DRUG INTERACTIONS

7.1 CYP3A4 Inhibitors and Inducers

Moderate or Strong CYP3A4 Inhibitors
The active metabolite of deflazacort, 21-desDFZ, is a substrate of CYP3A4 [see Clinical Pharmacology (12.3)]. Co-administration of deflazacort with clarithromycin, a strong CYP3A4 inhibitor, increased total exposure to 21-desDFZ by about 3-fold. Therefore, give one third the recommended dosage of EMFLAZA when moderate or strong CYP3A4 inhibitors (e.g., clarithromycin, fluconazole, diltiazem, verapamil, grapefruit juice) are used concomitantly with EMFLAZA [see Dosage and Administration (2.5) and Clinical Pharmacology (12.3)].

Moderate or Strong CYP3A4 Inducers
Co-administration of deflazacort with rifampin, a strong CYP3A4 inducer, significantly decreased the exposure of 21-desDFZ. Avoid concomitant use of strong (e.g., efavirenz) or moderate (e.g., carbamazepine, phenytoin) CYP3A4 inducers with EMFLAZA [see Dosage and Administration (2.5) and Clinical Pharmacology (12.3)].

7.2 Neuromuscular Blockers

Patients receiving corticosteroids, including EMFLAZA, and concomitant therapy with neuromuscular blocking drugs (e.g., pancuronium) may be at increased risk of developing an acute myopathy [see Warnings and Precautions (5.11)].

8 USE IN SPECIFIC POPULATIONS

8.1 Pregnancy

Risk Summary
Corticosteroids should be used during pregnancy only if the potential benefit justifies the potential risk to the fetus. Infants born to mothers who have received substantial doses of corticosteroids during pregnancy should be carefully observed for signs of hypoadrenalism. There are no adequate and well-controlled studies with EMFLAZA in pregnant women to inform drug-associated risks.

Corticosteroids, including EMFLAZA, readily cross the placenta. Adverse developmental outcomes, including orofacial clefts (cleft lip, with or without cleft palate) and intrauterine growth restriction, and decreased birth weight, have been reported with maternal use of corticosteroids, including EMFLAZA, during pregnancy. Some epidemiologic studies report an increased risk of orofacial clefts from about 1 per 1000 infants to 3 to 5 per 1000 infants; however, a risk for orofacial clefts has not been observed in all studies. Intrauterine growth restriction and decreased birth weight appear to be dose-related; however, the underlying maternal condition may also contribute to these risks (see Data). The estimated background risk of major birth defects and miscarriage for the indicated populations is unknown. In the U.S. general population, the estimated background risk of major birth defects and miscarriage in clinically recognized pregnancies is 2-4% and 15-20%, respectively.

Animal reproduction studies have not been conducted with deflazacort. Animal reproduction studies conducted with other corticosteroids in pregnant mice, rats, hamsters, and rabbits using clinically relevant doses have shown an increased incidence of cleft palate. An increase in embryofetal death, intrauterine growth retardation, and constriction of the ductus arteriosus were observed in some animal species.

Data
Human Data
Multiple cohort and case-controlled studies in humans suggest that maternal corticosteroid use during the first trimester increases the rate of cleft lip, with or without cleft palate, from about 1/1000 infants to 3-5/1000 infants. Two prospective case-controlled studies showed decreased birth weight in infants exposed to maternal corticosteroids in utero.

8.2 Lactation

Risk Summary
Systemically administered corticosteroids appear in human milk and could suppress growth, interfere with endogenous corticosteroid production, or cause other untoward effects. The developmental and health benefits of breastfeeding should be considered along with the mother’s clinical need for EMFLAZA and any potential adverse effects on the breastfed infant from EMFLAZA. There are no data on the effects on milk production.

8.4 Pediatric Use

The safety and effectiveness of EMFLAZA for the treatment of DMD have been established in patients 2 years of age and older. Use of EMFLAZA in pediatric patients is supported by a multicenter, randomized, double-blind, placebo- and active-controlled study in 196 males 5 to 15 years of age [see Clinical Studies (14)]. Use of EMFLAZA in patients 2 years to less than 5 years of age is supported by the findings of efficacy and safety in patients 5 years and older with DMD.

Safety and effectiveness in pediatric patients below the age of 2 years have not been established.

EMFLAZA Oral Suspension contains benzyl alcohol and is not approved for use in pediatric patients less than 2 years of age. Serious adverse reactions including fatal reactions and “gasping syndrome” occurred in premature neonates and low birth weight infants in the neonatal intensive care unit who received drugs containing benzyl alcohol as a preservative. In these cases, benzyl alcohol dosages of 99 to 234 mg/kg/day produced high levels of benzyl alcohol and its metabolites in the blood and urine (blood levels of benzyl alcohol were 0.61 to 1.378 mmol/L). Additional adverse reactions included gradual neurological deterioration, seizures, intracranial hemorrhage, hematologic abnormalities, skin breakdown, hepatic and renal failure, hypotension, bradycardia, and cardiovascular collapse. Preterm, low-birth weight infants may be more likely to develop these reactions because they may be less able to metabolize benzyl alcohol.

When prescribing EMFLAZA Oral Suspension consider the combined daily metabolic load of benzyl alcohol from all sources including EMFLAZA Oral Suspension (EMFLAZA Oral Suspension contains 10.45 mg of benzyl alcohol per mL; EMFLAZA Tablets do not contain benzyl alcohol) and other drugs containing benzyl alcohol. The minimum amount of benzyl alcohol at which serious adverse reactions may occur is not known. At the recommended dose of 0.9 mg/kg/day of EMFLAZA Oral Suspension, patients would receive approximately 0.4 mg/kg/day of benzyl alcohol [see Warnings and Precautions (5.13)].

Juvenile Animal Toxicity Data
Oral administration of deflazacort (0, 0.1, 0.3, and 1.0 mg/kg/day) to juvenile rats from postnatal day (PND) 21 to 80 resulted in decreased body weight gain and adverse effects on skeletal development (including decreased cellularity of growth plate and altered bone distribution) and on lymphoid tissue (decreased cellularity). A no-effect dose was not identified. In addition, neurological and neurobehavioral abnormalities were observed at the mid and/or high dose. Plasma 21-desDFZ exposure (AUC) at the lowest dose tested (0.1 mg/kg/day) was lower than that in humans at the recommended human dose of EMFLAZA (0.9 mg/kg/day).

8.5 Geriatric Use

DMD is largely a disease of children and young adults; therefore, there is no geriatric experience with EMFLAZA.

8.6 Renal Impairment

No dose adjustment is required in patients with mild, moderate or severe renal impairment [see Clinical Pharmacology (12.3)].

8.7 Hepatic Impairment

No dose adjustment is required in patients with mild or moderate hepatic impairment [see Clinical Pharmacology (12.3)]. There is no clinical experience in patients with severe hepatic impairment, and a dosing recommendation cannot be provided for patients with severe hepatic impairment.

10 OVERDOSAGE

Treatment of acute overdosage is by immediate gastric lavage or emesis followed by supportive and symptomatic therapy. For chronic overdosage in the face of severe disease requiring continuous steroid therapy, the dosage of EMFLAZA may be reduced temporarily, or alternate day treatment may be introduced.

11 DESCRIPTION

The active ingredient in EMFLAZA is deflazacort (a corticosteroid). Corticosteroids are adrenocortical steroids, both naturally occurring and synthetic. The molecular formula for deflazacort is C25H31NO6. The chemical name for deflazacort is (11β,16β)-21-(acetyloxy)-11-hydroxy-2'-methyl-5'H-pregna-1,4-dieno[17,16-d]oxazole-3,20-dione, and the structure is:

Deflazacort is a white to off white, odorless fine powder and has a molecular weight of 441.517. Deflazacort is freely soluble in acetic acid and dichloromethane and soluble in methanol and acetone.

EMFLAZA for oral administration is available as an immediate-release tablet in strengths of 6, 18, 30 and 36 mg and an immediate-release oral suspension in a strength of 22.75 mg/mL. Each tablet contains deflazacort and the following inactive ingredients: colloidal silicon dioxide, lactose monohydrate, magnesium stearate, and pre-gelatinized corn starch. The oral suspension contains deflazacort and the following inactive ingredients: acetic acid, aluminum magnesium silicate, benzyl alcohol, carboxymethylcellulose sodium, polysorbate 80, purified water, and sorbitol.

12 CLINICAL PHARMACOLOGY

12.1 Mechanism of Action

Deflazacort is a corticosteroid prodrug, whose active metabolite, 21-desDFZ, acts through the glucocorticoid receptor to exert anti-inflammatory and immunosuppressive effects. The precise mechanism by which deflazacort exerts its therapeutic effects in patients with DMD is unknown.

12.3 Pharmacokinetics

Absorption
After oral administration in the fasted state, the median Tmax with deflazacort tablets or suspension is about 1 hour (range 0.25 to 2 hours).

Food Effect: Co-administration of deflazacort tablets with a high-fat meal reduced Cmax by about 30% and delayed Tmax by one hour, relative to administration under fasting conditions, but there was no effect on the overall systemic absorption as measured by AUC. The bioavailability of deflazacort tablets was similar to that of the oral suspension. The administration of deflazacort with food or crushed in applesauce did not affect the absorption and bioavailability of deflazacort.

Distribution
The protein binding of the active metabolite of deflazacort is about 40%.

Elimination
Metabolism
Deflazacort is rapidly converted to the active metabolite 21-desDFZ by esterases after oral administration. 21-desDFZ is further metabolized by CYP3A4 to several other inactive metabolites, including 6β-hydroxy-21-desacetyl deflazacort.

Excretion
Urinary excretion is the predominant route of deflazacort elimination (about 68% of the dose), and the elimination is almost completed by 24 hours post dose. 21-desDFZ accounts for 18% of the eliminated drug in the urine.

Specific Populations
Pediatric Patients
The Cmax values (Geometric mean, %CV) of 21-desDFZ in children (ages 4-11, N=16) and adolescents (ages 12-16, N=8) was 206 ng/mL (95.6%) and 381 ng/mL (37.7%), respectively, on Day 1 after administration of 0.9 mg/kg deflazacort. The AUCinf (Geometric mean, %CV) of 21-desDFZ in children (ages 4-11, N=16) and adolescents (ages 12-16, N=8) was 400 ng•h/mL (87.5%) and 655 ng•h/mL (58.1%) on Day 1 after administration of 0.9 mg/kg deflazacort.

Male and Female Patients
There are no differences in the pharmacokinetics of 21-desDFZ between males and females.

Racial or Ethnic Groups
There are no differences in the pharmacokinetics of 21-desDFZ between Caucasians and non-Caucasians.

Patients with Renal Impairment
In a study (N=16) comparing subjects with end stage renal disease (creatinine clearance less than 15 mL/min) with healthy matched controls, 21-desDFZ exposure was similar between the groups.

Patients with Hepatic Impairment
In a study (N=16) comparing subjects with moderate hepatic impairment (Child-Pugh Class B) with healthy matched controls, 21-desDFZ exposure was similar between the groups. There is no experience in patients with severe hepatic impairment.

Drug Interaction Studies

In Vivo Assessment of Drug Interactions

Compared to administration of deflazacort alone, administration of deflazacort following multiple doses of a strong CYP3A4 and Pgp inhibitor (clarithromycin) resulted in markedly higher Cmax, AUClast, and AUCinf values of 21-desDFZ. Geometric mean exposure (Cmax, AUClast, and AUCinf) of 21-desDFZ ranged from 2.3-fold to 3.4-fold higher following administration of clarithromycin [see Dosage and Administration (2.5)].

Compared to administration of deflazacort alone, administration of deflazacort following multiple doses of a strong CYP3A4 inducer (rifampicin) resulted in markedly lower Cmax, AUClast, and AUCinf values of 21-desDFZ. Geometric mean exposures (Cmax, AUClast, and AUCinf) of 21-desDFZ were approximately 95% lower following administration of rifampin [see Drug Interactions (7.1)].

6β-Hydroxy-21-desacetyl deflazacort, a secondary and inactive metabolite, is not expected to cause any clinically meaningful interactions with the CYP enzymes or transporters.

In Vitro Assessment of Drug Interactions

Drug-Metabolizing Enzyme Inhibition
21-desDFZ at clinically relevant concentrations did not inhibit CYP1A2, 2C9, 2C19, 3A4, UGT1A1, UGT1A4, UGT1A6, UGT1A9, or UGT2B7 and exhibited weak and not likely clinically meaningful inhibition for 2B6, 2C8, 2D6, and 3A4, UGT1A3 and UGT2B15.

6β-Hydroxy-21-desacetyl deflazacort at clinically relevant concentrations did not significantly inhibit CYP2C19, 3A4 1A2, 2B6, 2C8, 2C9, or 2D6.

Drug-Metabolizing Enzyme Induction
21-desDFZ and 6β-hydroxy-21-desacetyl deflazacort at clinically relevant concentrations did not significantly induce CYP1A2, 2B6, or 3A4.

Transporters
Both deflazacort and 21-desDFZ are substrates of Pgp. 21-desDFZ is not a substrate for BCRP. Neither deflazacort nor 21-desDFZ inhibited Pgp or BCRP in vitro. 21-desDFZ was not a substrate for SLC transporters OATP1B1 or OATP1B3, and did not inhibit SLC transporters OATP1B1, OATP1B3, OAT1, OAT3, or OCT2.

6β-Hydroxy-21-desacetyl deflazacort at clinically relevant concentrations did not significantly inhibit BCRP, OAT1, OAT3, Pgp, OATP1B1, OATP1B3 MATE1, MATE2-K, OCT1, OCT2, or BSEP transporters.

13 NONCLINICAL TOXICOLOGY

13.1 Carcinogenesis, Mutagenesis, Impairment of Fertility

Carcinogenesis
In a published 2-year carcinogenicity study in rats, oral administration of deflazacort (0, 0.03, 0.06, 0.12, 0.25, 0.50, or 1.0 mg/kg/day) resulted in bone tumors (osteosarcoma and osteoma) of the head at 0.25 mg/kg/day, the highest evaluable dose. Doses higher than 0.25 mg/kg/day could not be evaluated for tumors because of a marked decrease in survival.

In a 6-month carcinogenicity study in transgenic (Tg.RasH2) mice, oral administration of deflazacort (0, 2, 5, or 20 mg/kg/day in males; 0, 0.5, 2, or 5 mg/kg/day in females) resulted in an increase in stomach tumors (adenoma) at the highest dose tested in males and females.

Mutagenesis
Deflazacort and 21-desDFZ were negative in in vitro (bacterial reverse mutation and human lymphocyte chromosomal aberration) assays and deflazacort was negative in an in vivo (rat micronucleus) assay.

Impairment of Fertility
Fertility studies in animals were not conducted with deflazacort. No effects on the male reproductive system were observed following oral administration of deflazacort to monkeys (0, 1.0, 3.0, or 6.0 mg/kg/day) for 39 weeks or rats (0, 0.05, 0.15, or 0.5 mg/kg/day) for 26 weeks. Plasma 21-desDFZ exposures (AUC) at the highest doses tested in monkey and rat were 4 and 2 times, respectively, that in humans at the recommended human dose of EMFLAZA (0.9 mg/kg/day).

14 CLINICAL STUDIES

The effectiveness of EMFLAZA for the treatment of DMD was established in Study 1, a multicenter, randomized, double-blind, placebo-controlled, 52-week study conducted in the US and Canada. The study population consisted of 196 male pediatric patients 5 to 15 years of age with documented mutation of the dystrophin gene, onset of weakness before 5 years of age, and serum creatinine kinase activity at least 10 times the upper limit of normal (ULN) at some stage in their illness. Patients were randomized to therapy with deflazacort (0.9 or 1.2 mg/kg/day), an active comparator, or placebo. A comparison to placebo was made after 12 weeks of treatment. After 12 weeks, placebo patients were re-randomized to receive either deflazacort or the active comparator; all patients continued treatment for an additional 40 weeks. Baseline characteristics were comparable between the treatment arms.

In Study 1, efficacy was evaluated by assessing the change between Baseline and Week 12 in average strength of 18 muscle groups. Individual muscle strength was graded using a modified Medical Research Council (MRC) 11-point scale, with higher scores representing greater strength.

The change in average muscle strength score between Baseline and Week 12 was significantly greater for the deflazacort 0.9 mg/kg/day dose group than for the placebo group (see Table 2).

Table 2: Analysis of Change from Baseline at Week 12 in Average Muscle Strength Score (Study 1)
Treatment | N | Change from Baseline LS Mean (95% CI) | P-value
Deflazacort 0.9 mg/kg/day | 51 | 0.15 (0.01, 0.28) | 0.017
Placebo | 50 | -0.10 (-0.23, 0.03)

Compared with the deflazacort 0.9 mg/kg/day group, the deflazacort 1.2 mg/kg/day group demonstrated a small additional benefit compared to placebo at Week 12, but had a greater incidence of adverse reactions. Therefore, use of a 1.2 mg/kg/day dosage of EMFLAZA is not recommended [see Dosage and Administration (2.2)].

Although not a pre-specified statistical analysis, compared with placebo, the deflazacort 0.9 mg/kg/day dose group demonstrated at Week 52 the persistence of the treatment effect observed at Week 12 and the small advantage of the 1.2 mg/kg/day dose that was observed at Week 12 was no longer present. Also not statistically controlled for multiple comparisons, results on several timed measures of patient function (i.e., time to stand from supine, time to climb 4 stairs, and time to walk or run 30 feet) numerically favored deflazacort 0.9 mg/kg/day at Week 12, in comparison with placebo.

An additional randomized, double-blind, placebo-controlled, 104-week clinical trial evaluated deflazacort in comparison to placebo (Study 2). The study population consisted of 29 male children 6 to 12 years of age with a DMD diagnosis confirmed by the documented presence of abnormal dystrophin or a confirmed mutation of the dystrophin gene. The results of the analysis of the primary endpoint of average muscle strength scores in Study 2 (graded on a 0-5 scale) at 2 years were not statistically significant, possibly because of a limited number of patients remaining in the placebo arm (subjects were discontinued from the trial when they lost ambulation). Although not statistically controlled for multiple comparisons, average muscle strength scores at Months 6 and 12, as well as the average time to loss of ambulation, numerically favored deflazacort in comparison with placebo.

16 HOW SUPPLIED/STORAGE AND HANDLING

16.1 How Supplied

EMFLAZA Tablets

- 6 mg are white, round with “6” debossed on one side. They are supplied as follows:
  NDC 52856-501-01 Bottle of 100 tablets
- 18 mg are white, round with “18” debossed on one side. They are supplied as follows:
  NDC 52856-502-03 Bottle of 30 tablets
- 30 mg are white, oval with “30” debossed on one side. They are supplied as follows:
  NDC 52856-503-03 Bottle of 30 tablets
- 36 mg are white, oval with “36” debossed on one side. They are supplied as follows:
  NDC 52856-504-03 Bottle of 30 tablets

EMFLAZA Oral Suspension

- 22.75 mg/mL is a whitish colored suspension. Supplied as 13 mL in a 30 mL bottle packaged with one bottle adapter and two 1 mL oral dispensers.
  NDC 52856-505-22

16.2 Storage and Handling

Store at 20°C to 25°C (68°F to 77°F). Excursion permitted between 15°C to 30°C (59°F to 86°F). See USP controlled room temperature.

Discard any unused EMFLAZA Oral Suspension remaining after 1 month of first opening the bottle.

17 PATIENT COUNSELING INFORMATION

Advise the patients and/or caregivers to read the FDA-approved patient labeling if EMFLAZA Oral Suspension is prescribed (Instructions for Use).

Administration

- Warn patients and/or caregivers to not stop taking EMFLAZA abruptly or without first checking with their healthcare providers as there may be a need for gradual dose reduction to decrease the risk of adrenal insufficiency [see Dosage and Administration (2.3) and Warnings and Precautions (5.1)].
- EMFLAZA may be taken with or without food. Do not take EMFLAZA with grapefruit juice.

Tablets

- EMFLAZA Tablets may be taken whole or crushed and taken immediately after mixing with applesauce.

Oral Suspension

- EMFLAZA Oral Suspension must be shaken well prior to measuring out each dose with the enclosed oral dispenser.
- The EMFLAZA Oral Suspension dose may be placed in 3-4 ounces of juice (except grapefruit juice) or milk, mixed thoroughly, and immediately administered.
- Discard any unused EMFLAZA Oral Suspension remaining after 1 month of first opening the bottle.

Increased Risk of Infection
Tell patients and/or caregivers to inform their healthcare provider if the patient has had recent or ongoing infections or if they have recently received a vaccine. Medical advice should be sought immediately if the patient develops fever or other signs of infection. Patients and/or caregivers should be made aware that some infections can potentially be severe and fatal.

Warn patients who are on corticosteroids to avoid exposure to chickenpox or measles and to alert their healthcare provider immediately if they are exposed [see Warnings and Precautions (5.2)].

Alterations in Cardiovascular/Renal Function
Inform patients and/or caregivers that EMFLAZA can cause an increase in blood pressure and water retention. If this occurs, dietary salt restriction and potassium supplementation may be needed [see Warnings and Precautions (5.3)].

Behavioral and Mood Disturbances
Advise patients and/or caregivers about the potential for severe behavioral and mood changes with EMFLAZA and encourage them to seek medical attention if psychiatric symptoms develop [see Warnings and Precautions (5.5)].

Decreases in Bone Mineral Density
Advise patients and/or caregivers about the risk of osteoporosis with prolonged use of EMFLAZA, which can predispose the patient to vertebral and long bone fractures [see Warnings and Precautions (5.6)].

Ophthalmic Effects
Inform patients and/or caregivers that EMFLAZA may cause cataracts or glaucoma and advise monitoring if corticosteroid therapy is continued for more than 6 weeks [see Warnings and Precautions (5.7)].

Vaccination
Advise patients and/or caregivers to bring immunizations up-to-date according to immunization guidelines prior to starting therapy with EMFLAZA. Live-attenuated or live vaccines should be administered at least 4 to 6 weeks prior to starting EMFLAZA. Inform patients and/or caregivers that they may receive concurrent vaccinations with use of EMFLAZA, except for live-attenuated or live vaccines. [see Warnings and Precautions (5.8)].

Serious Skin Rashes
Instruct patients and/or caregivers to seek medical attention at the first sign of a rash [see Warnings and Precautions (5.9)].

Drug Interactions
Certain medications can cause an interaction with EMFLAZA. Advise patients and/or caregivers to inform their healthcare provider of all the medicines the patient is taking, including over-the-counter medicines (such as insulin, aspirin or other NSAIDS), dietary supplements, and herbal products. Inform patients and/or caregivers that alternate therapy, dosage adjustment, and/or special test(s) may be needed during the treatment.

PTC Therapeutics

Manufactured for:
PTC Therapeutics, Inc.
Warren, NJ 07059 U.S.A.

EMFLAZA Oral Suspension made in Spain

EMFLAZA® is a trademark of PTC Therapeutics, Inc.

Instructions for Use
EMFLAZA™ (em fla' zah)
(deflazacort)
oral suspension

Read this Instructions for Use before you start using EMFLAZA oral suspension and each time you get a refill. There may be new information. This information does not take the place of talking to your healthcare provider about your medical condition or treatment.

Important information before you use EMFLAZA oral suspension:

- Only use the oral dispenser (see Figure A below) that comes in your EMFLAZA carton when using this medicine.
- EMFLAZA oral suspension can be taken with or without food.
- Take your dose of EMFLAZA oral suspension with juice or milk. Do not take EMFLAZA with grapefruit juice.
- Throw away (discard) any unused EMFLAZA oral suspension after 1 month of first opening the bottle.
- Do not stop taking EMFLAZA oral suspension without talking to your healthcare provider first.

Preparing for your EMFLAZA oral suspension dose:

You will need the following supplies: See Figure A.

- 1 EMFLAZA oral suspension bottle
- 1 oral dispenser (2 oral dispensers are included in the EMFLAZA oral suspension carton. 1 is to be used to give (administer) the product and 1 extra oral dispenser is included as a spare, if needed.)
- 1 household cup filled with 3 to 4 ounces of juice or milk
- 1 spoon

Figure A

How to prepare your dose of EMFLAZA oral suspension:

Step 1. Remove the EMFLAZA oral suspension bottle and 1 of the oral dispensers from the carton.

Step 2. Make sure the bottle cap is put on tightly and shake well before each use. See Figure B.

Figure B

Step 3. Remove the cap from the bottle by pushing down firmly on the cap and turning the cap in a counter-clockwise direction (to the left). See Figure C. Place the open bottle upright on a flat surface.

Figure C

First time use of bottle only:
Unwrap the bottle adapter.
Place the ribbed end of the bottle adapter in the bottle top.
Wrap both hands around the bottle. Press down on the bottle adapter using both thumbs. Push the ribbed end of the bottle adapter firmly into the neck of the bottle until the adapter top is even with the bottle top. See Figure D.
Do not remove the bottle adapter from the bottle after it is inserted.
Write the date that you first open the bottle on the bottle label.

Figure D

Step 4. Unwrap the oral dispenser if it is the first time you are using the oral dispenser.
Check your dose in milliliters (mL) as prescribed by your healthcare provider. Find this number on the barrel of the oral dispenser. See Figure E.

Figure E

The oral dispenser only holds 1 mL of medicine at a time. If your dose is more than 1 mL, you will need to repeat Steps 5 through 8 using the same oral dispenser until your entire dose has been drawn from the bottle.

Step 5. Push the plunger of the oral dispenser all the way down. Insert the oral dispenser into the bottle adapter. See Figure F.

Figure F

Step 6. With the oral dispenser in the bottle adapter, carefully turn the bottle upside down. Slowly pull back on the plunger until the widest part of the plunger is at the line marking on the oral dispenser of the number of mL needed for your dose. See Figure G. Do not use the narrow tip on the end of the plunger to measure the dose.

If you see air bubbles in the oral suspension, fully push in the plunger so the oral suspension flows back into the bottle. Then withdraw the dose of oral suspension that you need.

Figure G

Step 7. Leave the oral dispenser in the bottle adapter and turn the bottle to an upright position. Place the bottle onto a flat surface. Remove the oral dispenser from the bottle adapter by gently twisting the oral dispenser while pulling it straight up. See Figure H.

Figure H

Step 8. Slowly push all the way down on the plunger of the oral dispenser to add the EMFLAZA oral suspension dose to a household cup filled with 3 to 4 ounces of juice or milk. See Figure I.

Figure I

Step 9. Stir the EMFLAZA oral suspension and juice or milk with a spoon to mix well. See Figure J.

Figure J

Step 10. Immediately drink the juice or milk that is mixed with EMFLAZA oral suspension.

Step 11. Replace the cap tightly on the bottle by turning the cap in a clockwise direction (to the right). See Figure K.

Figure K

Step 12. Wash the oral dispenser after each use. The oral dispenser should be taken apart by pulling back on the plunger and removing it from the barrel of the oral dispenser. See Figure L.

Figure L

Step 13. After the barrel and plunger are dry, put the oral dispenser back together by pushing the plunger back into the barrel.

How should I store EMFLAZA oral suspension?

- Store the bottle upright at room temperature between 68°F to 77°F (20°C to 25°C).
- Throw away (discard) any unused EMFLAZA oral suspension after 1 month of first opening the bottle.

What are the ingredients in EMFLAZA oral suspension?
Active ingredient: deflazacort
Inactive ingredients: acetic acid, aluminum magnesium silicate, benzyl alcohol, carboxymethylcellulose sodium, polysorbate 80, purified water, and sorbitol.

Manufactured for: PTC Therapeutics, Inc., Warren, NJ 07059, U.S.A.

This Instructions for Use has been approved by the U.S. Food and Drug Administration. EMFLAZA™ is a trademark of PTC Therapeutics, Inc.

20EMF13891961118

Revised: 06/2024

PRINCIPAL DISPLAY PANEL - NDC: 52856-501-01 - 6 mg Tablet 100-Count Bottle Label

NDC 52856-501-01
100 Tablets
Emflaza™
(deflazacort)
Tablets
for oral use
6 mg
Rx Only

PRINCIPAL DISPLAY PANEL - NDC: 52856-501-01 - 6 mg Tablet 100-Count Carton Label

NDC 52856-501-01
100 Tablets
Emflaza™
(deflazacort)
Tablets
for oral use
6 mg
Rx Only

PRINCIPAL DISPLAY PANEL - NDC: 52856-502-03 - 18 mg Tablet 30-Count Bottle Label

NDC 52856-502-03
30 Tablets
Emflaza™
(deflazacort)
Tablets
for oral use
18 mg
Rx Only

PRINCIPAL DISPLAY PANEL - NDC: 52856-502-03 - 18 mg Tablet 30-Count Carton Label

NDC 52856-502-03
30 Tablets
Emflaza™
(deflazacort)
Tablets
for oral use
18 mg
Rx Only

PRINCIPAL DISPLAY PANEL - NDC: 52856-503-03 - 30 mg Tablet 30-Count Bottle Label

NDC 52856-503-03
30 Tablets
Emflaza™
(deflazacort)
Tablets
for oral use
30 mg
Rx Only

PRINCIPAL DISPLAY PANEL - NDC: 52856-503-03 - 30 mg Tablet 30-Count Carton Label

NDC 52856-503-03
30 Tablets
Emflaza™
(deflazacort)
Tablets
for oral use
30 mg
Rx Only

PRINCIPAL DISPLAY PANEL - NDC: 52856-504-03 - 36 mg Tablet 30-Count Bottle Label

NDC 52856-504-03
30 Tablets
Emflaza™
(deflazacort)
Tablets
for oral use
36 mg
Rx Only

PRINCIPAL DISPLAY PANEL - NDC: 52856-504-03 - 36 mg Tablet 30-Count Carton Label

NDC 52856-504-03
30 Tablets
Emflaza™
(deflazacort)
Tablets
for oral use
36 mg
Rx Only

PRINCIPAL DISPLAY PANEL - NDC: 52856-505-22 - 22.75 mg/mL Oral Suspension 13 mL Bottle Label

NDC 52856-505-22
13 mL
Emflaza®
(deflazacort)
Oral Suspension
Rx only
22.75 mg/mL
For Oral Administration Only

PRINCIPAL DISPLAY PANEL - NDC: 52856-505-22 - 22.75 mg/mL Oral Suspension 13 mL Carton Label

NDC 52856-505-22
13 mL
Emflaza®
(deflazacort)
Oral Suspension
22.75 mg/mL
For Oral Administration Only
Rx only